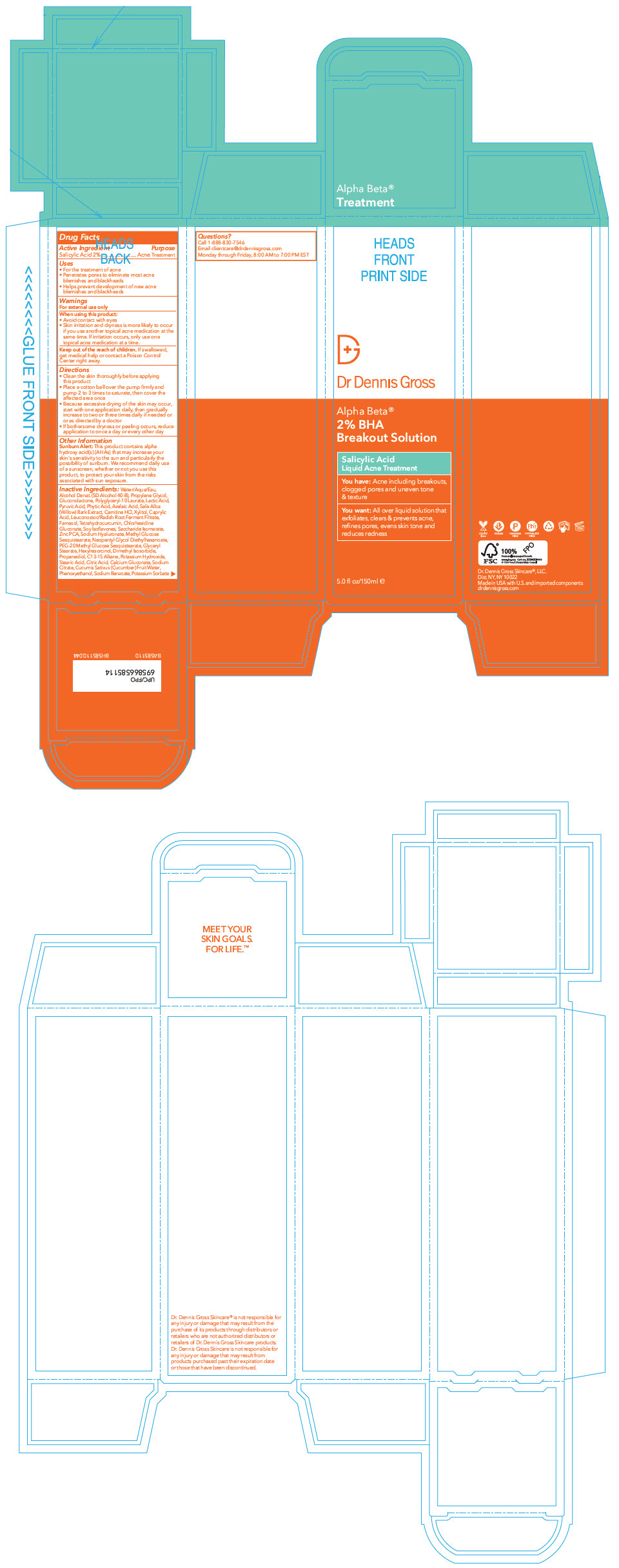 DRUG LABEL: Dr. Gross AB Acne Daily Breakout
NDC: 51326-179 | Form: LIQUID
Manufacturer: Topiderm, Inc
Category: otc | Type: HUMAN OTC DRUG LABEL
Date: 20231120

ACTIVE INGREDIENTS: SALICYLIC ACID 20 mg/1 mL
INACTIVE INGREDIENTS: WATER; GLUCONOLACTONE; CARNITINE; SALIX ALBA BARK; FYTIC ACID; LACTIC ACID, DL-; PYRUVIC ACID; AZELAIC ACID; ZINC PIDOLATE; ALCOHOL; POTASSIUM HYDROXIDE; GENISTEIN; HEXYLRESORCINOL; TETRAHYDROCURCUMIN .BETA.-O-GLUCURONIDE; CHLORHEXIDINE GLUCONATE; POLYGLYCERYL-10 LAURATE; FARNESOL; LEVOCARNITINE HYDROCHLORIDE; HYALURONATE SODIUM; LEUCONOSTOC/RADISH ROOT FERMENT FILTRATE; NEOPENTYL GLYCOL DIETHYLHEXANOATE; SACCHARIDE ISOMERATE; DIMETHYL ISOSORBIDE; GLYCERYL MONOSTEARATE; METHYL GLUCOSE SESQUISTEARATE; PEG-20 METHYL GLUCOSE SESQUISTEARATE; CUCUMBER FRUIT OIL; XYLITOL; CAPRYLIC ACID; SODIUM BENZOATE; C13-15 ALKANE; CALCIUM GLUCONATE; TERT-BUTYL ALCOHOL; DENATONIUM BENZOATE; ANHYDROUS CITRIC ACID; SODIUM CITRATE, UNSPECIFIED FORM; POTASSIUM SORBATE; PHENOXYETHANOL; .ALPHA.-TOCOPHEROL; STEARIC ACID; PROPANEDIOL

Dr. Gross AB Acne Daily Breakout

Drug Facts

Active Ingredient

Salicylic Acid 2%

Purpose

Acne Treatment

Uses

- For the treatment of acne
- Penetrates pores to eliminate most acne blemishes and blackheads
- Helps prevent development of new acne blemishes and blackheads

Warnings

For external use only

When using this product

- Avoid contact with eyes
- Skin irritation and dryness is more likely to occur if you use another topical acne medication at the same time. If irritation occurs, only use one topical acne medication at a time.

Keep out of reach of children. If swallowed, get medical help or contact a Poison Control Center right away.

Directions

- Clean the skin thoroughly before applying this product
- Place a cotton ball over the pump firmly and pump 2 to 3 times to saturate, then cover the affected area once
- Because excessive drying of the skin may occur, start with one application daily, then gradually increase to two or three times daily if needed or or as directed by a doctor
- If bothersome dryness or peeling occurs, reduce application to once a day or every other day

Other Information

Sunburn Alert

This product contains alpha hydroxy acid(s) (AHAs) that may increase your skin's sensitivity to the sun and particularly the possibility of sunburn. We recommend daily use of a sunscreen, whether or not you use this product, to protect your skin from the risks associated with sun exposure.

Inactive Ingredients

Water/Aqua/Eau, Alcohol Denat. (SD Alcohol 40-B), Propylene Glycol, Gluconolactone, Polyglyceryl-10 Laurate, Lactic Acid, Pyruvic Acid, Phytic Acid, Azelaic Acid, Salix Alba (Willow) Bark Extract, Carnitine HCl, Xylitol, Caprylic Acid, Leuconostoc/Radish Root Ferment Filtrate, Farnesol, Tetrahydrocurcumin, Chlorhexidine Gluconate, Soy Isoflavones, Saccharide Isomerate, Zinc PCA, Sodium Hyaluronate, Methyl Glucose Sesquistearate, Neopentyl Glycol Diethylhexanoate, PEG-20 Methyl Glucose Sesquistearate, Glyceryl Stearate, Hexylresorcinol, Dimethyl Isosorbide, Propanediol, C13-15 Alkane, Potassium Hydroxide, Stearic Acid, Citric Acid, Calcium Gluconate, Sodium Citrate, Cucumis Sativus (Cucumber) Fruit Water, Phenoxyethanol, Sodium Benzoate, Potassium Sorbate

Questions?

Call 1-888-830-7546

Email clientcare@drdennisgross.com

Monday through Friday, 8:00 AM to 7:00 PM EST

PRINCIPAL DISPLAY PANEL - 150 ml Bottle Carton

Dr Dennis Gross

Alpha Beta®
2% BHA
Breakout Solution

Salicylic Acid
Liquid Acne Treatment

You have: Acne including breakouts,
clogged pores and uneven tone
& texture

You want: All over liquid solution that
exfoliates, clears & prevents acne,
refines pores, evens skin tone and
reduces redness

5.0 fl oz/150ml ℮